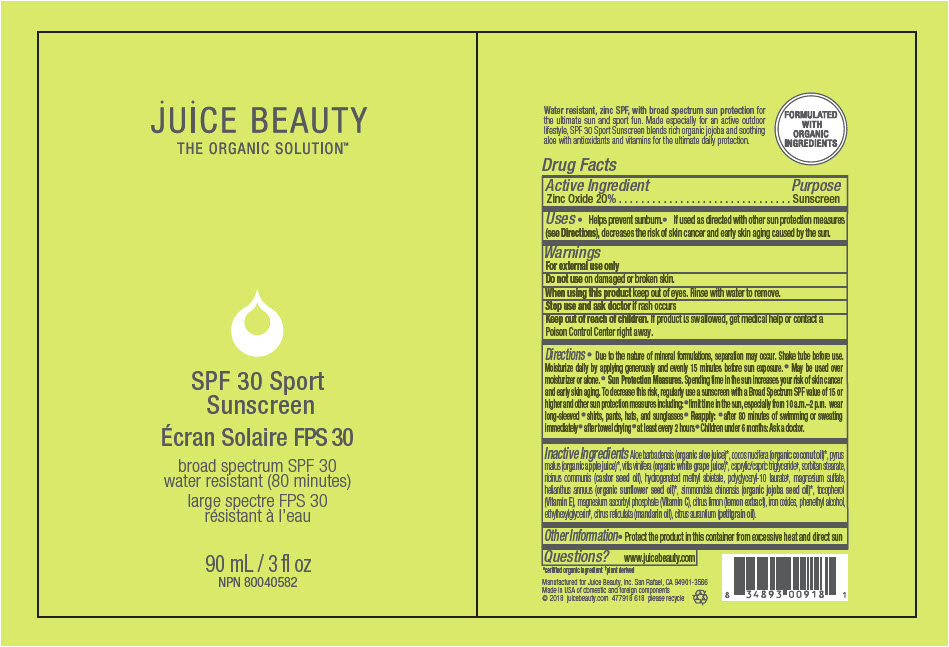 DRUG LABEL: SPF 30 Sport Sunscreen
NDC: 55165-0204 | Form: LOTION
Manufacturer: Juice Beauty
Category: otc | Type: HUMAN OTC DRUG LABEL
Date: 20241223

ACTIVE INGREDIENTS: Zinc Oxide 20 g/100 mL
INACTIVE INGREDIENTS: apple juice; WINE GRAPE; ALOE VERA LEAF; coconut oil; MEDIUM-CHAIN TRIGLYCERIDES; SORBITAN MONOSTEARATE; CASTOR OIL; polyglyceryl-10 laurate; MAGNESIUM SULFATE, UNSPECIFIED FORM; HELIANTHUS ANNUUS FLOWERING TOP; jojoba oil; tocopherol; MAGNESIUM ASCORBYL PHOSPHATE; Hydrogenated Methyl Abietate; LEMON; FERRIC OXIDE YELLOW; FERRIC OXIDE RED; FERROSOFERRIC OXIDE; PHENYLETHYL ALCOHOL; ethylhexylglycerin; mandarin oil; CITRUS AURANTIUM LEAFY TWIG OIL

SPF 30 Sport Sunscreen

Drug Facts

Active Ingredient

Zinc Oxide 20%

Purpose

Sunscreen

Uses

- Helps prevent sunburn.
- If used as directed with other sun protection measures (see Directions), decreases the risk of skin cancer and early skin aging caused by the sun.

Warnings

For external use only

Do not use on damaged or broken skin.

When using this product keep out of eyes. Rinse with water to remove.

Stop use and ask doctor if rash occurs

Keep out of reach of children. If product is swallowed, get medical help or contact a Poison Control Center right away.

Directions

- Due to the nature of mineral formulations, separation may occur. Shake tube before use. Moisturize daily by applying generously and evenly 15 minutes before sun exposure.
- May be used over moisturizer or alone.
- Sun Protection Measures. Spending time in the sun increases your risk of skin cancer and early skin aging. To decrease this risk, regularly use a sunscreen with a Broad Spectrum SPF value of 15 or higher and other sun protection measures including:
  - limit time in the sun, especially from 10 a.m.–2 p.m. wear long-sleeved
  - shirts, pants, hats, and sunglasses
- Reapply:
  - after 80 minutes of swimming or sweating immediately
  - after towel drying
  - at least every 2 hours
- Children under 6 months: Ask a doctor.

Inactive Ingredients

Aloe barbadensis (organic aloe juice) [certified organic ingredient] , cocos nucifera (organic coconut oil), pyrus malus (organic apple juice), vitis vinifera (organic white grape juice), caprylic/capric triglyceride [plant derived] , sorbitan stearate, ricinus communis (castor seed oil), hydrogenated methyl abietate, polyglyceryl-10 laurate, magnesium sulfate, helianthus annuus (organic sunflower seed oil), simmondsia chinensis (organic jojoba seed oil), tocopherol (Vitamin E), magnesium ascorbyl phosphate (Vitamin C), citrus limon (lemon extract), iron oxides, phenethyl alcohol, ethylhexylglycerin, citrus reticulata (mandarin oil), citrus aurantium (petitgrain oil).

Other Information

- Protect the product in this container from excessive heat and direct sun

Questions?

www.juicebeauty.com

PRINCIPAL DISPLAY PANEL - 90 mL Tube Label

jUiCE BEAUTY
THE ORGANIC SOLUTION™

SPF 30 Sport
Sunscreen

broad spectrum SPF 30
water resistant (80 minutes)

90 mL / 3 fl oz
NPN 80040582